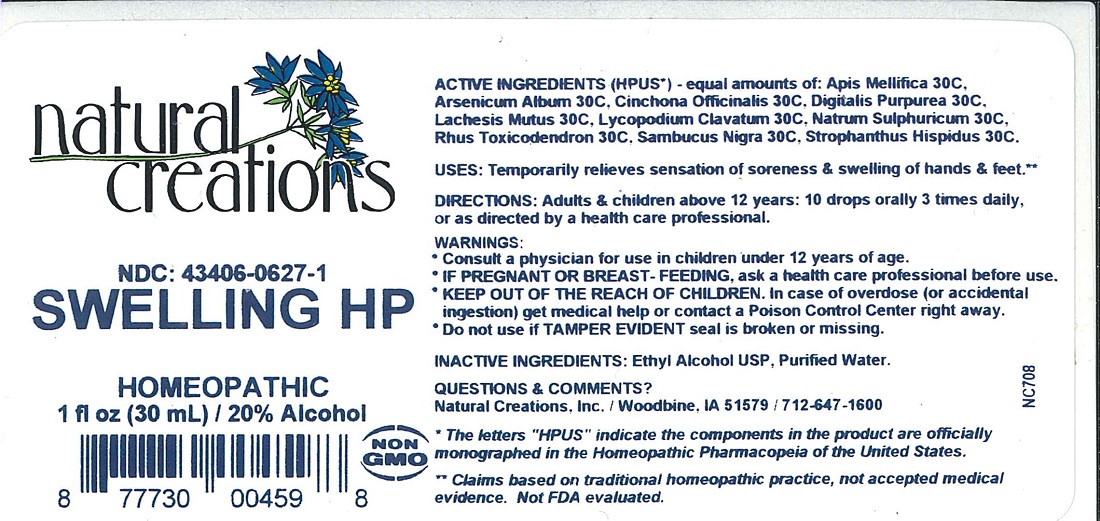 DRUG LABEL: SWELLING HP
NDC: 43406-0627 | Form: LIQUID
Manufacturer: Natural Creations, Inc.
Category: homeopathic | Type: HUMAN OTC DRUG LABEL
Date: 20221219

ACTIVE INGREDIENTS: APIS MELLIFERA 30 [hp_C]/1 mL; ARSENIC TRIOXIDE 30 [hp_C]/1 mL; CINCHONA OFFICINALIS BARK 30 [hp_C]/1 mL; DIGITALIS 30 [hp_C]/1 mL; LACHESIS MUTA VENOM 30 [hp_C]/1 mL; LYCOPODIUM CLAVATUM SPORE 30 [hp_C]/1 mL; SODIUM SULFATE 30 [hp_C]/1 mL; TOXICODENDRON PUBESCENS LEAF 30 [hp_C]/1 mL; SAMBUCUS NIGRA FLOWERING TOP 30 [hp_C]/1 mL; STROPHANTHUS HISPIDUS SEED 30 [hp_C]/1 mL
INACTIVE INGREDIENTS: WATER; ALCOHOL

SWELLING HP

ACTIVE INGREDIENT

ACTIVE INGREDIENTS (HPUS*) - equal amounts of: Apis Mellifica 30C, Arsenicum Album 30C, Cinchona Officinalis 30C, Digitalis Purpurea 30C, Lachesis Mutus 30C, Lycopodium Clavatum 30C, Natrum Sulphuricum 30C, Rhus Toxicodendron 30C, Sambucus Nigra 30C, Strophanthus Hispidus 30C

INDICATIONS AND USAGE

USES: Temporarily relieves sensation of soreness & swelling of hands & feet.**

WARNING:

*Consult a physician for use in children under 12 years of age.

*IF PREGNANT OR BREAST-FEEDING, ask a health care professional before use.

*KEEP OUT OF THE REACH OF CHILDREN. In case of overdose (or accidental ingestion) get medical help or contact a Poison Control Center

right away.

*Do not use if TAMPER EVIDENT seal is broken or missing.

DOSAGE AND ADMINISTRATION

DIRECTIONS: Adults and children above 12 years: 10 drops orally 3 times daily, or as directed by a health care professional.

REFERENCES

*The letters "HPUS" indicate the components in the product are officially monographed in the Homeopathic Pharmacopeia of the United States.

**Claims based on traditional homeopathic practice, not accepted medical evidence. Not FDA evaluated.

INACTIVE INGREDIENTS: Ethyl Acohol USP, Purified Water.

QUESTIONS AND COMMENTS?

Natural Creations, Inc. / Woodbine, IA 51579 / 712-647-1600

PURPOSE

USES: Temporarily relieves sensation of soreness & swelling of hands & feet.**

KEEP OUT OF REACH OF CHILDREN

KEEP OUT OF THE REACH OF CHILDREN. In case of overdose (or accidental ingestion) get medical help or contact a Poison Control Center.

PACKAGE LABEL

NDC: 43406-0627-1

SWELLING HP

HOMEOPATHIC

1 fl oz (30 mL) / 20% Alcohol

UPC: 877730004598 NON GMO Logo